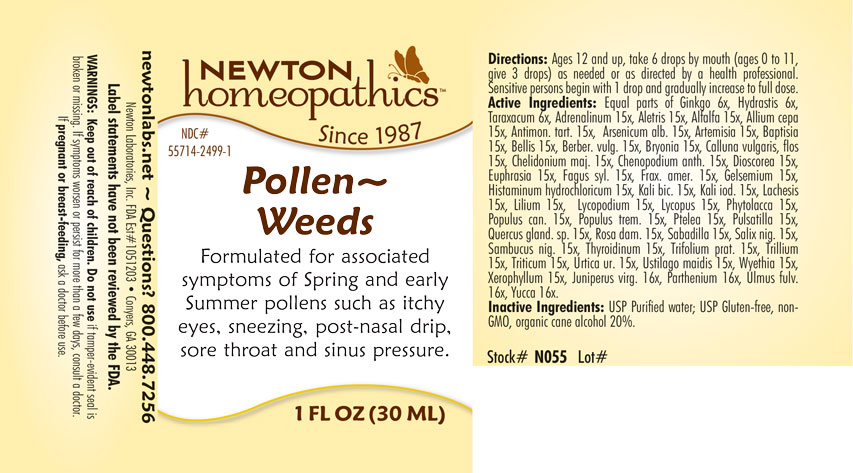 DRUG LABEL: Pollen-Weeds
NDC: 55714-2499 | Form: LIQUID
Manufacturer: Newton Laboratories, Inc.
Category: homeopathic | Type: HUMAN OTC DRUG LABEL
Date: 20250207

ACTIVE INGREDIENTS: PARTHENIUM HYSTEROPHORUS 16 [hp_X]/1 mL; XEROPHYLLUM ASPHODELOIDES 15 [hp_X]/1 mL; EPINEPHRINE 15 [hp_X]/1 mL; ALFALFA 15 [hp_X]/1 mL; ALETRIS FARINOSA ROOT 15 [hp_X]/1 mL; ARTEMISIA VULGARIS ROOT 15 [hp_X]/1 mL; BELLIS PERENNIS 15 [hp_X]/1 mL; DYSPHANIA AMBROSIOIDES 15 [hp_X]/1 mL; LYCOPUS VIRGINICUS 15 [hp_X]/1 mL; PHYTOLACCA AMERICANA ROOT 15 [hp_X]/1 mL; POPULUS BALSAMIFERA LEAF BUD 15 [hp_X]/1 mL; POPULUS TREMULOIDES LEAF 15 [hp_X]/1 mL; PTELEA TRIFOLIATA BARK 15 [hp_X]/1 mL; SAMBUCUS NIGRA FLOWERING TOP 15 [hp_X]/1 mL; TRILLIUM ERECTUM ROOT 15 [hp_X]/1 mL; ELYMUS REPENS ROOT 15 [hp_X]/1 mL; URTICA URENS 15 [hp_X]/1 mL; WYETHIA HELENIOIDES ROOT 15 [hp_X]/1 mL; YUCCA FILAMENTOSA 16 [hp_X]/1 mL; HISTAMINE DIHYDROCHLORIDE 15 [hp_X]/1 mL; JUNIPERUS VIRGINIANA TWIG 16 [hp_X]/1 mL; THYROID, UNSPECIFIED 15 [hp_X]/1 mL; USTILAGO MAYDIS 15 [hp_X]/1 mL; ONION 15 [hp_X]/1 mL; ANTIMONY POTASSIUM TARTRATE 15 [hp_X]/1 mL; ARSENIC TRIOXIDE 15 [hp_X]/1 mL; BAPTISIA TINCTORIA ROOT 15 [hp_X]/1 mL; BERBERIS VULGARIS ROOT BARK 15 [hp_X]/1 mL; BRYONIA ALBA ROOT 15 [hp_X]/1 mL; CHELIDONIUM MAJUS 15 [hp_X]/1 mL; EUPHRASIA STRICTA 15 [hp_X]/1 mL; GELSEMIUM SEMPERVIRENS ROOT 15 [hp_X]/1 mL; POTASSIUM DICHROMATE 15 [hp_X]/1 mL; POTASSIUM IODIDE 15 [hp_X]/1 mL; LACHESIS MUTA VENOM 15 [hp_X]/1 mL; LYCOPODIUM CLAVATUM SPORE 15 [hp_X]/1 mL; ANEMONE PULSATILLA 15 [hp_X]/1 mL; SCHOENOCAULON OFFICINALE SEED 15 [hp_X]/1 mL; DIOSCOREA VILLOSA TUBER 15 [hp_X]/1 mL; GINKGO 6 [hp_X]/1 mL; TARAXACUM OFFICINALE 6 [hp_X]/1 mL; GOLDENSEAL 6 [hp_X]/1 mL; QUERCUS ROBUR NUT 15 [hp_X]/1 mL; CALLUNA VULGARIS FLOWERING TOP 15 [hp_X]/1 mL; ULMUS RUBRA BARK 16 [hp_X]/1 mL; FAGUS SYLVATICA NUT 15 [hp_X]/1 mL; FRAXINUS AMERICANA BARK 15 [hp_X]/1 mL; LILIUM LANCIFOLIUM WHOLE FLOWERING 15 [hp_X]/1 mL; ROSA DAMASCENA FLOWERING TOP 15 [hp_X]/1 mL; TRIFOLIUM PRATENSE FLOWER 15 [hp_X]/1 mL; SALIX NIGRA BARK 15 [hp_X]/1 mL
INACTIVE INGREDIENTS: WATER; ALCOHOL

Pollen 2499L

INDICATIONS & USAGE SECTION

Formulated for associated symptoms of Spring and early Summer pollens such as itchy eyes, sneezing, post-nasal drip, sore throat and sinus pressure.

DOSAGE & ADMINISTRATION SECTION

Directions: Ages 12 and up, take 6 drops by mouth (ages 0 to 11, give 3 drops) as needed or as directed by a health professional. Sensitive persons begin with 1 drop and gradually increase to full dose.

OTC - ACTIVE INGREDIENT SECTION

Equal parts of Ginkgo biloba 6x, Hydrastis canadensis 6x, Taraxacum officinale 6x, Adrenalinum 15x, Aletris farinosa 15x, Alfalfa 15x, Allium cepa 15x, Antimonium tartaricum 15x, Arsenicum album 15x, Artemisia vulgaris 15x, Baptisia tinctoria 15x, Bellis perennis 15x, Berberis vulgaris 15x, Bryonia 15x, Calluna vulgaris, flos 15x, Chelidonium majus 15x, Chenopodium anthelminticum 15x, Dioscorea vilosa 15x, Euphrasia officinalis 15x, Fagus sylvatica 15x, Fraxinus americana 15x, Gelsemium sempervirens 15x, Histaminum hydrochloricum 15x, Kali bichromicum 15x, Kali iodatum 15x, Lachesis mutus 15x, Lilium tigrinum 15x, Lycopodium clavatum 15x, Lycopus virginicus 15x, Phytolacca decandra 15x, Populus candicans 15x, Populus tremuloides 15x, Ptelea trifoliata 15x, Pulsatilla 15x, Quercus glandium spiritus 15x, Rosa damascena 15x, Sabadilla 15x, Salix nigra 15x, Sambucus nigra 15x, Thyroidinum 15x, Trifolium pratense 15x, Trillium pendulum 15x, Triticum repens 15x, Urtica urens 15x, Ustilago maidis 15x, Wyethia helenoides 15x, Xerophyllum asphodeloides 15x, Juniperus virginiana 16x, Parthenium 16x, Ulmus fulva 16x, Yucca filamentosa 16x.

OTC - PURPOSE SECTION

Formulated for associated symptoms of Spring and early Summer pollens such as itchy eyes, sneezing, post-nasal drip, sore throat and sinus pressure.

INACTIVE INGREDIENT SECTION

Inactive Ingredients: USP Purified Water; USP Gluten-free, non-GMO, organic cane dispensing alcohol 20%.

QUESTIONS SECTION

newtonlabs.net – Questions? 800.448.7256

Newton Laboratories, Inc. FDA Est # 1051203 - Conyers, GA 30013

WARNINGS SECTION

Warnings: Keep out of reach of children. Do no use if tamper-evident seal is broken or missing. If symptoms worsen or persist for more than a few days, consult a doctor. If pregnant or breast-feeding, ask a doctor before use.

OTC - PREGNANCY OR BREAST FEEDING SECTION

If pregnant or breast-feeding, ask a doctor before use.

OTC - KEEP OUT OF REACH OF CHILDREN SECTION

Keep out of reach of children.